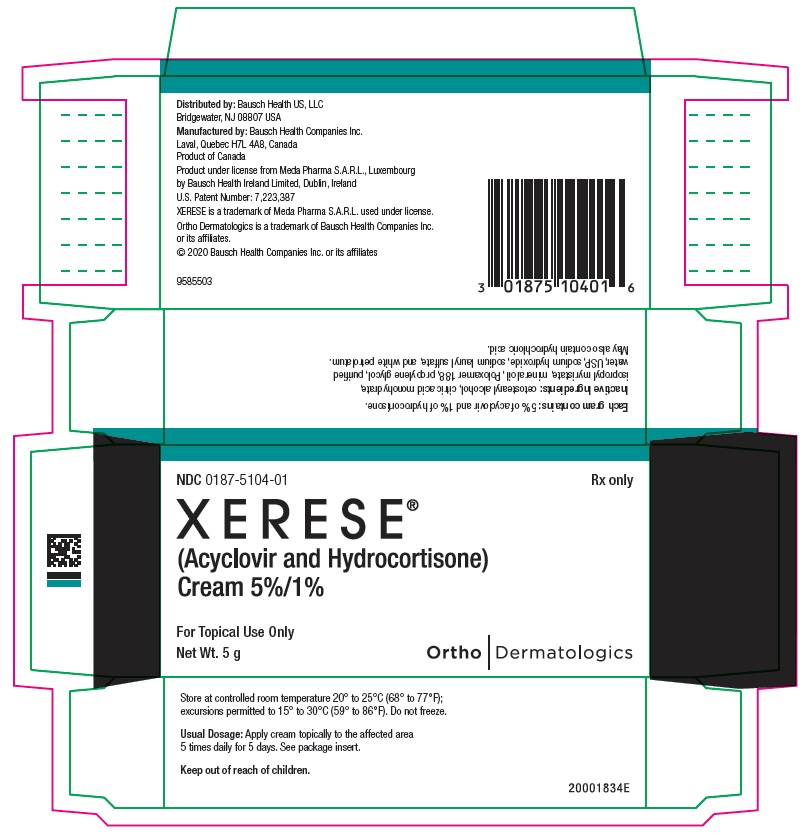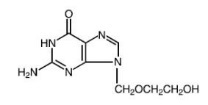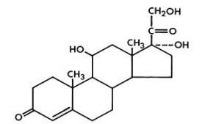 DRUG LABEL: Xerese
NDC: 0187-5104 | Form: CREAM
Manufacturer: Bausch Health US LLC
Category: prescription | Type: HUMAN PRESCRIPTION DRUG LABEL
Date: 20200803

ACTIVE INGREDIENTS: ACYCLOVIR 50 mg/1 g; HYDROCORTISONE 10 mg/1 g
INACTIVE INGREDIENTS: cetostearyl alcohol; mineral oil; Poloxamer 188; propylene glycol; isopropyl myristate; sodium lauryl sulfate; petrolatum; citric acid monohydrate; sodium hydroxide; water; HYDROCHLORIC ACID

HIGHLIGHTS OF PRESCRIBING INFORMATION

These highlights do not include all the information needed to use XERESE safely and effectively. See full prescribing information for XERESE.
XERESE® (acyclovir and hydrocortisone) cream, for topical use
Initial U.S. Approval: 2009

1 INDICATIONS AND USAGE

XERESE, a combination of acyclovir, a herpes simplex virus deoxynucleoside analog DNA polymerase inhibitor, and hydrocortisone, a corticosteroid, is indicated for the early treatment of recurrent herpes labialis (cold sores) to reduce the likelihood of ulcerative cold sores and to shorten the lesion healing time in adults and children (6 years of age and older). (1)

2 DOSAGE AND ADMINISTRATION

Topically apply XERESE 5 times per day for 5 days. Therapy should be initiated as early as possible after the first signs and symptoms (i.e., during the prodrome or when lesions appear). (2)

3 DOSAGE FORMS AND STRENGTHS

Cream: 50 mg (equivalent to 5%, w/w) acyclovir and 10 mg (equivalent to 1%, w/w) hydrocortisone. (3)

4 CONTRAINDICATIONS

None. (4)

5 WARNINGS AND PRECAUTIONS

- Only for topical use for recurrent herpes labialis on the lips and around the mouth. (5)

6 ADVERSE REACTIONS

The following most common adverse reactions (<1%) were local skin reactions:

Drying or flaking of the skin; burning or tingling, erythema; pigmentation changes; application site reactions including signs and symptoms of inflammation. (6.1)

To report SUSPECTED ADVERSE REACTIONS, contact Bausch Health US, LLC at 1-800-321-4576 or FDA at 1-800-FDA-1088 or www.fda.gov/medwatch.

7 DRUG INTERACTIONS

No drug interaction studies have been performed with XERESE. (7)

8 USE IN SPECIFIC POPULATIONS

Immunocompromised Patients: Benefit has not been adequately assessed. (8.6)

FULL PRESCRIBING INFORMATION

1 INDICATIONS AND USAGE

XERESE, a combination of acyclovir, a herpes simplex virus deoxynucleoside analog DNA polymerase inhibitor, and hydrocortisone, a corticosteroid, is indicated for the early treatment of recurrent herpes labialis (cold sores) to reduce the likelihood of ulcerative cold sores and to shorten the lesion healing time in adults and children (6 years of age and older).

2 DOSAGE AND ADMINISTRATION

Topically apply XERESE 5 times per day for 5 days. Therapy should be initiated as early as possible after the first signs and symptoms (i.e., during the prodrome or when lesions appear).

For each dose, topically apply a quantity of XERESE sufficient to cover the affected area, including the outer margin. Avoid unnecessary rubbing of the affected area to avoid aggravating or transferring the infection. For children 6 years of age and older, the dosage is the same as in adults.

3 DOSAGE FORMS AND STRENGTHS

Each gram of XERESE contains 50 mg (equivalent to 5%, w/w) acyclovir and 10 mg (equivalent to 1%, w/w) hydrocortisone in an aqueous cream base.

4 CONTRAINDICATIONS

None.

5 WARNINGS AND PRECAUTIONS

5.1 General

XERESE is intended for cutaneous use only for herpes labialis of the lips and around the mouth. XERESE should not be used in the eye, inside the mouth or nose, or on the genitals.

There are other orofacial lesions, including bacterial and fungal infections, which may be difficult to distinguish from a cold sore. Patients should be encouraged to seek medical advice when a cold sore fails to heal within 2 weeks.

XERESE has a potential for irritation and contact sensitization [see Adverse Reactions (6.1)].

6 ADVERSE REACTIONS

6.1 Adverse Reactions in Clinical Trials

Because clinical trials are conducted under widely varying conditions, the adverse reaction rates observed cannot be directly compared to rates in other clinical trials and may not reflect the rates observed in clinical practice.

The safety data derived from XERESE clinical trials reflect exposure to XERESE in 1,056 subjects with recurrent herpes labialis treated 5 times daily for 5 days.

The most common adverse reactions (<1%) were local skin reactions, and occurred in the area of the application site, including:

- Drying or flaking of the skin; burning or tingling following application; erythema; pigmentation changes; application site reaction including signs and symptoms of inflammation.

Contact dermatitis following application has been observed when applied under occlusion in dermal safety trials. Where contact sensitivity tests have been conducted, the reactive substances were hydrocortisone or a component of the cream base.

A trial enrolling 225 healthy adults was conducted to evaluate the contact sensitization potential of XERESE using repeat insult patch testing methodology. Of 205 evaluable subjects, one confirmed case (0.5%) of sensitization to hydrocortisone and 2 additional cases (1.0%) of possible sensitization to the XERESE base were identified. Additionally, one subject developed a contact allergy in the photosafety study to propylene glycol, one of the inactive ingredients of the cream base.

Dermal tolerance was assessed in a 21-day cumulative irritation trial in 36 healthy subjects. XERESE, its cream base and Zovirax® (acyclovir) Cream 5% all showed a high and cumulative irritation potential under occlusive and semi-occlusive conditions.

Photoallergic potential and phototoxicity were assessed in two trials in 50 and 30 healthy volunteers, respectively. No photoallergic or phototoxicity potential was identified for XERESE.

7 DRUG INTERACTIONS

No drug interaction studies have been performed with XERESE.

8 USE IN SPECIFIC POPULATIONS

8.1 Pregnancy

Risk Summary

There are no available data on XERESE use in pregnant women. However, published observational studies over decades of use of topical acyclovir and low and medium potency topical corticosteroids during pregnancy have not established any association between use of these products and major birth defects, miscarriage, or adverse maternal or fetal outcomes (see Data).

Animal reproduction studies have not been conducted with XERESE. Systemic exposure of acyclovir and hydrocortisone following topical administration of XERESE is expected to be minimal. Animal reproduction studies with systemic exposure of acyclovir and hydrocortisone have been conducted. Refer to acyclovir and hydrocortisone prescribing information for additional details.

The estimated background risk of major birth defects and miscarriage for the indicated population is unknown. All pregnancies have a background risk of birth defect, loss, or other adverse outcomes. In the U.S. general population, the estimated background risk of major birth defects and miscarriage in clinically recognized pregnancies is 2% to 4% and 15% to 20%, respectively.

Data

Human Data

While available studies cannot definitively establish the absence of risk, published data from multiple large observational studies have not established an association with the use of topical acyclovir or low and medium potency topical corticosteroids (including hydrocortisone) during pregnancy and major birth defects, miscarriage, or adverse maternal or fetal outcomes. Available studies have methodological limitations including whether women who filled a prescription actually took the medication, non-randomized design, retrospective data collection, and the inability to control for confounders such as underlying maternal disease and use of concomitant medications.

8.2 Lactation

Risk Summary
There are no data on the presence of acyclovir or hydrocortisone in human milk following topical administration. There are no data on the effects of acyclovir or hydrocortisone on the breastfed infant or on milk production. Systemic exposure following topical administration of either drug is expected to be minimal. The developmental and health benefits of breastfeeding should be considered along with the mother’s clinical need for XERESE and any potential adverse effects on the breastfed child from XERESE or from the underlying maternal condition.

8.4 Pediatric Use

Safety and effectiveness in pediatric subjects less than 6 years of age have not been established.

8.5 Geriatric Use

In clinical studies, there were insufficient subjects above 65 years of age to reach a firm conclusion regarding safety and efficacy of XERESE in this group, although the available results were similar to lower age subjects.

8.6 Immunocompromised Subjects

Even though the safety of XERESE has been studied in immunocompromised subjects, data are insufficient to support use in this population. Immunocompromised subjects should be encouraged to consult a physician concerning the treatment of any infection.

Benefit has not been adequately assessed in immunocompromised patients. A randomized, double-blind trial was conducted in 107 immunocompromised subjects with stable HIV infection and recurrent herpes labialis. Subjects had on average 3.7 episodes of herpes labialis in the previous 12 months. The median age was 30 years (range 19 to 64 years), 46% were female, and all Caucasian. Median CD4+ T-cell count at screening was 344/mm^3 (range 100-500/mm^3). Subjects were treated with XERESE or 5% acyclovir in XERESE vehicle. The primary objective was to exclude a doubling of the healing time in either treatment arm. The mean healing time for cold sores was similar between the two treatment groups: 6.6 days for XERESE and 6.9 days for 5% acyclovir in XERESE vehicle.

10 OVERDOSAGE

Overdosage by topical application of XERESE is unlikely because of minimal systemic exposure [see Clinical Pharmacology (12.3)].

11 DESCRIPTION

XERESE contains acyclovir, a synthetic nucleoside analogue active against herpes viruses, and hydrocortisone, an anti-inflammatory corticosteroid, combined in a cream for topical administration. Each gram of XERESE contains 50 mg (equivalent to 5%, w/w) of acyclovir, 10 mg (equivalent to 1%, w/w) of hydrocortisone and the following inactive ingredients: cetostearyl alcohol, citric acid monohydrate, isopropyl myristate, mineral oil, Poloxamer 188, propylene glycol, purified water, USP, sodium hydroxide, sodium lauryl sulfate, and white petrolatum. Sodium hydroxide or hydrochloric acid may have been added to adjust the pH to approximately pH 5.

Acyclovir, 2-Amino-9-[(2-hydroxyethoxy)methyl]-1,9-dihydro-6H-purin-6-one, is a synthetic nucleoside analogue active against herpes viruses. The maximum solubility of acyclovir in water at 37°C is 2.5 mg/mL. The pKa’s of acyclovir are 2.27 and 9.25. Its empirical formula is C8H11N5O3. The structural formula is provided in Figure 1:

Figure 1: Structural Formula of Acyclovir

Hydrocortisone, pregn-4-ene-3,20-dione, 11,17,21-trihydroxy- (11β), is an anti-inflammatory corticosteroid. Its empirical formula is C21H30O5. The structural formula is provided in Figure 2:

Figure 2: Structural Formula of Hydrocortisone

12 CLINICAL PHARMACOLOGY

12.1 Mechanism of Action

Acyclovir is an antiviral drug active against α-herpesviruses and hydrocortisone is an anti-inflammatory drug [see Microbiology (12.4)].

12.3 Pharmacokinetics

The plasma concentrations of acyclovir and hydrocortisone were not measured following topical administration of XERESE on cold sores.

The extent of percutaneous absorption of topical corticosteroids is determined by many factors including the vehicle, the integrity of the epidermal barrier, and the use of occlusive dressings.

Topical corticosteroids can be absorbed from normal intact skin and can have systemic side effects depending on both the potency of the corticosteroid and the surface area of application. Inflammation and/or other disease processes in the skin that disrupt the skin barrier can increase percutaneous absorption.

Once absorbed through the skin, topical corticosteroids are handled through pharmacokinetic pathways similar to systemically administered corticosteroids. Corticosteroids are bound to plasma proteins in varying degrees. They are metabolized primarily in the liver and are then excreted by the kidneys. Some of the topical corticosteroids and their metabolites are also excreted into the bile.

12.4 Microbiology

Mechanism of Action
Acyclovir is a synthetic purine deoxynucleoside analogue with inhibitory activity against herpes simplex viruses type 1 (HSV-1) and type 2 (HSV-2) DNA polymerases. It inhibits HSV-1 and HSV-2 replication in cell culture and in vivo.
The inhibitory activity of acyclovir is selective due to its affinity for the enzyme thymidine kinase (TK) encoded by HSV. This viral enzyme converts acyclovir into acyclovir monophosphate, a deoxynucleotide analogue. The monophosphate is further converted into diphosphate by cellular guanylate kinase and into triphosphate by a number of cellular enzymes. In biochemical assays, acyclovir triphosphate inhibits replication of α-herpes viral DNA. This inhibition is accomplished in 3 ways: 1) competitive inhibition of viral DNA polymerase, 2) incorporation into and termination of the growing viral DNA chain, and 3) inactivation of the viral DNA polymerase.
Hydrocortisone is the main glucocorticoid secreted by the adrenal cortex. It is used topically for its anti-inflammatory effects which suppress the clinical manifestations of the disease in a wide range of disorders where inflammation is a prominent feature.
Antiviral Activity
The quantitative relationship between the susceptibility of herpes viruses to antivirals in cell culture and the clinical response to therapy has not been established in humans, and virus sensitivity testing has not been standardized. Sensitivity testing results, expressed as the concentration of drug required to inhibit by 50% the growth of virus in cell culture (EC50 value), vary greatly depending upon a number of factors. Using plaque-reduction assays on Vero cells, the EC50 value of acyclovir against herpes virus isolates ranged from 0.09 to 60 µM (0.02 to 13.5 µg/mL) for HSV-1 and from 0.04 to 44 µM (0.01 to 9.9 µg/mL) for HSV-2.
Resistance
In Cell Culture
Acyclovir-resistant HSV-1 and HSV-2 strains were isolated in cell culture. Acyclovir-resistant HSV resulted from mutations in the viral thymidine kinase (TK; pUL23) and DNA polymerase (POL; pUL30) genes. Frameshifts were commonly isolated and result in premature truncation of the HSV TK product with consequent decreased susceptibility to acyclovir. Mutations in the viral TK gene may lead to complete loss of TK activity (TK negative), reduced levels of TK activity (TK partial), or alteration in the ability of viral TK to phosphorylate the drug without an equivalent loss in the ability to phosphorylate thymidine (TK altered). In cell culture the following resistance-associated substitutions in TK of HSV-1 and HSV-2 were observed (Table 1).

Table 1: Summary of Acyclovir (ACV) Resistance-associated Amino Acid Substitutions in Cell Culture
HSV-1 | TK | P5A, H7Q, L50V, G56V, G59A, G61A, K62N, T63A, E83K, P84S, D116N, P131S, R163H, A167V, P173L, Q185R, R216S, R220H, T245M, R281stop, T287M, M322K
HSV-2 | TK | L69P, C172R, T288M
HSV-1 | POL | D368A, Y557S, E597D, V621S, L702H, N815S, V817M, G841C
HSV-2 | POL | -

In HSV-Infected Patients
Clinical HSV-1 and HSV-2 isolates obtained from patients who failed treatment for their α-herpesvirus infections were evaluated for genotypic changes in the TK and POL genes and for phenotypic resistance to acyclovir (Table 2). HSV isolates with frameshift mutations and resistance-associated substitutions in TK and POL were identified. The listing of substitutions in HSV TK and POL leading to decreased susceptibility to acyclovir is not all inclusive and additional changes will likely be identified in HSV variants isolated from patients who fail acyclovir-containing regimens. The possibility of viral resistance to acyclovir should be considered in patients who fail to respond or experience recurrent viral shedding during therapy.

Table 2: Summary of ACV Resistance-associated Amino Acid Substitutions Observed in Treated Patients
HSV-1 | TK | G6C, R32H, R41H, R51W, Y53C/D/H, Y53stop, D55N, G56D/S, P57H, H58/N/R/Y, G59R, G61A, K62N, T63I, Q67stop, S74stop, Y80N, E83K, P84L, Y87H, W88R, R89Q/W, E95stop, T103P, Q104H, Q104stop, H105P, D116N, M121L/R, S123R, Q125H, M128L, G129D, I143V, A156V, D162A/H/N, R163G/H, L170P, Y172C, P173L, A174P, A175V, R176Q/W, R176stop, L178R, S181N, V187M, A189V, V192A, G200C/D/S, T201P, V204G, A207P, L208F/H, R216C/H, R220C/H, R221H, R222C/H, L227F, T245M/P, L249P, Q250Stop, C251G, R256W, E257K, Q261R, T287M, L288Stop, L291P/R, L297S, L315S, L327R, C336Y, Q342Stop, T354P, L364P, A365T
HSV-2 | TK | R34C, G39E, R51W, Y53N, G59P, G61W, S66P, A72S, D78N, P85S, A94V, N100H, I101S, Q105P, T131P, D137stop, F140L, L158P, S169P, R177W, S182N, M183I, V192M, G201D, R217H, R221C/H, Q222stop, R223H, Y239stop, R271V, P272S, D273R, T287M, C337Y
HSV-1 | POL | K532T, Q570R, L583V, A605V, A657T, D672N, V715G, A719T/V, S724N, F733C, E771Q, S775N, L778M, E798K, V813M, N815S, G841S, I890M, G901V, V958L H1228D
HSV-2 | POL | E250Q, D307N, K533E, A606V, C625R, R628C, E678G, A724V, S725G, S729N, I731F, Q732R, M789K/T, V818A, N820S, Y823C, Q829R, T843A, M910T, D912N/V, A915V, F923L, T934A, R964H

Note: Additional substitutions to acyclovir resistance may exist.

Cross-resistance
Cross-resistance has been observed among HSV isolates carrying frameshift mutations and resistance-associated substitutions, which confer reduced susceptibility to penciclovir (PCV), famciclovir (FCV), and foscarnet (FOS) [Table 3].

Table 3: Summary of Amino Acid Substitutions Conferring Cross-Resistance to PCV, FCV or FOS
Cross-resistant to PCV/FCV | HSV-1 TK | G6C, R32H, R51W, Y53C/H, H58N, G61A, S74Stop, E83K, P84L, T103P, Q104Stop, D116N, M121R, I143V, R163H, L170P, Y172C, A174P, R176Q/W, Q185R, A189V, G200D, L208H, R216C, R220H, R222C/H, T245M, Q250Stop, R256W, R281Stop, T287M, L315S, M322K, C336Y
Cross-resistant to PCV/FCV | HSV-1 POL | A657T, D672N, V715G, A719V, S724N, E798K, N815S, G841S
Cross-resistant to PCV/FCV | HSV-2 TK | G39E, R51W, Y53N, R177W, R221H, T288M
Cross-resistant to PCV/FCV | HSV-2 POL | K533E, A606V, C625R, R628C, S729N, Q732R, M789K/T, V818A, N820S, F923L, T934A
Cross-resistant to FOS | HSV-1 POL | D368A, A605V, D672N, L702H, V715G, A719T/V, S724N, L778M, E798K, V813M, N815S, V817M, G841C/S, I890M,
Cross-resistant to FOS | HSV-2 POL | K533E, A606V, C625R, R628C, A724V, S725G, S729N, I731F, Q732R, M789K/T, V818A, Y823C, D912V, F923L, T934A, R964H

13 NONCLINICAL TOXICOLOGY

13.1 Carcinogenesis, Mutagenesis, Impairment of Fertility

Systemic exposure following topical administration of acyclovir is minimal. Results from previous studies of carcinogenesis, mutagenesis and fertility for acyclovir and hydrocortisone are not included in the full prescribing information for XERESE due to the minimal exposures that result from dermal application. Information on these studies following systemic exposure is available in the full prescribing information for acyclovir and hydrocortisone products approved for oral or parenteral administration. Dermal carcinogenicity studies have not been conducted.

14 CLINICAL STUDIES

14.1 Clinical Trial Experience in Adults

In a double-blind, clinical trial, 1,443 subjects with recurrent labial herpes were randomized to receive XERESE, 5% acyclovir in XERESE vehicle or vehicle alone. Subjects had, on average, 5.6 episodes of herpes labialis in the previous 12 months. The median age was 44 years (range 18 to 80 years), 72% were female, and 91% were Caucasian. Subjects were instructed to initiate treatment within 1 hour of noticing signs or symptoms and continue treatment for 5 days, with application of study medication 5 times per day. Ulcerative cold sores occurred in 58% of the subjects treated with XERESE compared to 74% in subjects treated with vehicle and 65% in subjects treated with 5% acyclovir in XERESE vehicle. The mean time to skin normalization was approximately 1.6 days shorter in the subjects treated with XERESE compared to vehicle. Clinical signs in terms of size of the cold sore and symptoms such as tenderness were reduced with XERESE as compared to vehicle.

14.2 Clinical Trial Experience in Pediatric Subjects

An open-label safety trial in adolescents with recurrent herpes labialis was conducted in 134 subjects. Subjects had, on average, 4 episodes of herpes labialis in the previous 12 months. The median age was 14 years (range 12 to 17 years); 50% were female and all were Caucasian. XERESE was applied using the same dosing regimen as in adults and subjects were monitored for adverse events and selected efficacy parameters. The safety profile of XERESE appeared similar to that observed in adults.

An open-label safety trial in children with recurrent herpes labialis was conducted in 54 subjects, who averaged an episode of herpes labialis 2 months prior to trial entry. The mean age was 9 years (range 6 to 11 years); 57% were female and 90% were Caucasian. XERESE was applied using the same dosing regimen as in adolescents and adults and subjects were monitored for adverse events and select efficacy parameters. The safety profile of XERESE appeared similar to that observed in adults.

16 HOW SUPPLIED/STORAGE AND HANDLING

XERESE is supplied in a plastic-laminated aluminum tube containing 5 g of XERESE. Each gram of XERESE contains 50 mg (equivalent to 5%, w/w) acyclovir and 10 mg (equivalent to 1%, w/w) hydrocortisone in an aqueous cream base.

NDC 0187-5104-01 5 g tubes

Store at controlled room temperature 20° to 25°C (68° to 77°F); excursions permitted to 15° to 30°C (59° to 86°F). Do not freeze.

17 PATIENT COUNSELING INFORMATION

Advise the patient to read the FDA-approved patient labeling (Patient Information).

General

Patients should be informed that XERESE is not a cure for cold sores. Patients should be instructed that XERESE is intended for cutaneous use only for herpes labialis of the lips and around the mouth. Patients should be advised that XERESE should not be used in the eye, inside the mouth or nose, or on the genitals.

Instructions for Use

Advise patients to apply XERESE topically 5 times per day for 5 days. Instruct patients to topically apply a quantity of XERESE sufficient to cover the affected area, including the outer margin. Advise patients to avoid unnecessary rubbing of the affected area to avoid aggravating or transferring the infection.

Distributed by:

Bausch Health US, LLC

Bridgewater, NJ 08807 USA

Manufactured by:

Bausch Health Companies Inc.

Laval, Quebec H7L 4A8, Canada

Product under license from Meda Pharma S.A.R.L., Luxembourg by Bausch Health Ireland Limited, Dublin, Ireland

U.S. Patent Number: 7,223,387

XERESE is a trademark of Meda Pharma S.A.R.L. used under license.

Zovirax is a registered trademark of the GlaxoSmithKline group of companies.

© 2020 Bausch Health Companies Inc. or its affiliates

9587303

FDA-Approved Patient Labeling

PATIENT INFORMATION
XERESE® (sûr-eeze)
(acyclovir and hydrocortisone) Cream 5%/1%

Important information: XERESE is for use on cold sores on the lips and around the mouth only. XERESE should not be used in your eyes, mouth, nose or on your genitals.

What is XERESE?

- XERESE is a prescription medicine used in people 6 years of age and older to shorten the healing time of cold sores (herpes labialis) and lower the chance of a cold sore becoming worse (ulcerating).
- XERESE is not a cure for cold sores.

It is not known if XERESE is safe and effective in children less than 6 years of age.

What should I tell my healthcare provider before using XERESE?

Before using XERESE, tell your healthcare provider about all of your medical conditions, including if you:

- become sick very easily (have a weak immune system)
- are pregnant or plan to become pregnant. It is not known if XERESE will harm your unborn baby.
- are breastfeeding or plan to breastfeed. It is not known if XERESE passes into your breast milk. Talk with your healthcare provider about the best way to feed your baby if you use XERESE.

Tell your healthcare provider about all the medicines you take, including prescription and over-the-counter medicines, vitamins, and herbal supplements.

How should I use XERESE?

- Use XERESE exactly as your healthcare provider tells you to use it.
- Use XERESE as soon as you have the first symptom of a cold sore such as itching, redness, burning or tingling or when the cold sore appears.
- Apply XERESE over the affected area, including the outer edge of the cold sore.
- Do not rub the cold sore because this may cause the cold sore to spread to other areas around your mouth or make your cold sore worse.
- Do not cover the cold sore or the area around the cold sore with a bandage.
- Do not use other skin products (such as make-up, sun screen or lip balm) or other skin medicine on the cold sore or the area around the cold sore.
- Tell your healthcare provider if your cold sore is not better in 2 weeks.

What are the possible side effects of XERESE?
The most common side effects of XERESE are skin reactions at the treatment site and may include:

- drying or flaking, tingling or burning after you apply XERESE, redness, changes in skin color where the cream is applied, and swelling.

These are not all the possible side effects of XERESE. Call your doctor for medical advice about side effects. You may report side effects to FDA at 1-800-FDA-1088.

How should I store XERESE?

- Store XERESE at room temperature between 68° to 77°F (20° to 25°C). Do not freeze XERESE.

Keep XERESE and all medicines out of the reach of children.

General information about the safe and effective use of XERESE.

Medicines are sometimes prescribed for purposes other than those listed in a Patient Information leaflet. Do not use XERESE for a condition for which it was not prescribed. Do not give XERESE to other people, even if they have the same symptoms that you have. It may harm them. You can ask your pharmacist or healthcare provider for information about XERESE that is written for healthcare professionals.

What are the ingredients in XERESE?

Active ingredients: acyclovir and hydrocortisone

Inactive ingredients: cetostearyl alcohol, citric acid monohydrate, isopropyl myristate, mineral oil, Poloxamer 188, propylene glycol, sodium lauryl sulfate, purified water, USP, sodium hydroxide, and white petrolatum. May also contain hydrochloric acid.

Distributed by: Bausch Health US, LLC, Bridgewater, NJ 08807 USA

Manufactured by: Bausch Health Companies Inc., Laval, Quebec H7L 4A8, Canada

Product under license from Meda Pharma S.A.R.L., Luxembourg by Bausch Health Ireland Limited, Dublin, Ireland

U.S. Patent Number: 7,223,387

XERESE is a trademark of Meda Pharma S.A.R.L. used under license.

Zovirax is a registered trademark of the GlaxoSmithKline group of companies.

© 2020 Bausch Health Companies Inc. or its affiliates

For more information call 1-800-321-4576.

This Patient Information has been approved by the U.S. Food and Drug Administration.

Revised: 08/2020

9587303

PACKAGE LABEL

NDC 0187-5104-01

Rx only

XERESE®
(Acyclovir and Hydrocortisone)
Cream 5%/1%

For Topical Use Only

Net Wt. 5 g

Ortho Dermatologics